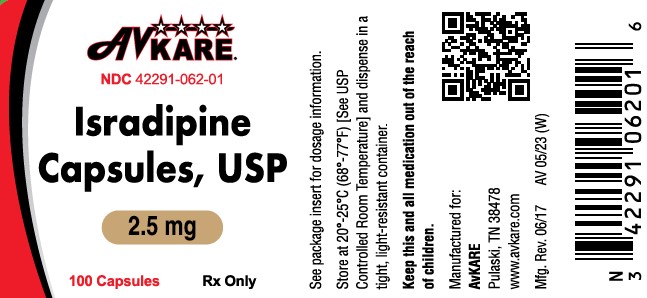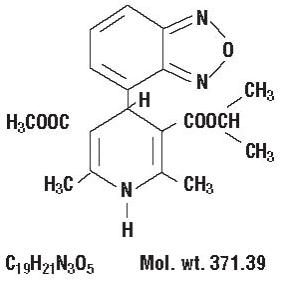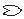 DRUG LABEL: Isradipine
NDC: 42291-062 | Form: CAPSULE
Manufacturer: AvKARE
Category: prescription | Type: HUMAN PRESCRIPTION DRUG LABEL
Date: 20260114

ACTIVE INGREDIENTS: ISRADIPINE 2.5 mg/1 1
INACTIVE INGREDIENTS: SILICON DIOXIDE; FERRIC OXIDE RED; FERRIC OXIDE YELLOW; GELATIN; ANHYDROUS LACTOSE; MAGNESIUM STEARATE; SODIUM LAURYL SULFATE; STARCH, CORN; TITANIUM DIOXIDE; FERROSOFERRIC OXIDE; SHELLAC; POTASSIUM HYDROXIDE

Isradipine Capsules, USP

DESCRIPTION

Isradipine is a calcium antagonist available for oral administration in capsules containing 2.5 mg or 5 mg.

The structural formula of isradipine is:

Chemically, isradipine is 3,5-Pyridinedicarboxylic acid, 4-(4-benzofurazanyl)-1,4-dihydro-2,6-dimethyl-, methyl 1-methylethyl ester. Isradipine is a yellow, fine crystalline powder which is odorless or has a faint characteristic odor. Isradipine is practically insoluble in water (<10 mg/L at 37ºC), but is soluble in ethanol and freely soluble in acetone, chloroform and methylene chloride.

Active Ingredient: isradipine

Inactive Ingredients: colloidal silicon dioxide, red iron oxide (2.5 mg capsule only), yellow iron oxide, gelatin, anhydrous lactose, magnesium stearate, sodium lauryl sulfate, starch (corn), titanium dioxide, black ink: black iron oxide, shellac and potassium hydroxide.

CLINICAL PHARMACOLOGY

Mechanism of Action

Isradipine is a dihydropyridine calcium channel blocker. It binds to calcium channels with high affinity and specificity and inhibits calcium flux into cardiac and smooth muscle. The effects observed in mechanistic experiments in vitro and studied in intact animals and man are compatible with this mechanism of action and are typical of the class.

Except for diuretic activity, the mechanism of which is not clearly understood, the pharmacodynamic effects of isradipine observed in whole animals can also be explained by calcium channel blocking activity, especially dilating effects in arterioles which reduce systemic resistance and lower blood pressure, with a small increase in resting heart rate. Although like other dihydropyridine calcium channel blockers, isradipine has negative inotropic effects in vitro, studies conducted in intact anesthetized animals have shown that the vasodilating effect occurs at doses lower than those which affect contractility. In patients with normal ventricular function, isradipine’s afterload reducing properties lead to some increase in cardiac output.

Effects in patients with impaired ventricular function have not been fully studied.

Clinical Effects

Dose-related reductions in supine and standing blood pressure are achieved within 2-3 hours following single oral doses of 2.5 mg, 5 mg, 10 mg, and 20 mg isradipine, with a duration of action (at least 50% of peak response) of more than 12 hours following administration of the highest dose.

Isradipine has been shown in controlled, double-blind clinical trials to be an effective antihypertensive agent when used as monotherapy, or when added to therapy with thiazide-type diuretics. During chronic administration, divided doses (b.i.d.) in the range of 5-20 mg daily have been shown to be effective, with response at trough (prior to next dose) over 50% of the peak blood pressure effect. The response is dose-related between 5-10 mg daily. Isradipine is equally effective in reducing supine, sitting, and standing blood pressure.

On chronic administration, increases in resting pulse rate averaged about 3-5 beats/min. These increases were not dose-related.

Hemodynamics

In man, peripheral vasodilation produced by isradipine is reflected by decreased systemic vascular resistance and increased cardiac output. Hemodynamic studies conducted in patients with normal left ventricular function produced, following intravenous isradipine administration, increases in cardiac index, stroke volume index, coronary sinus blood flow, heart rate, and peak positive left ventricular dP/dt. Systemic, coronary, and pulmonary vascular resistance was decreased. These studies were conducted with doses of isradipine which produced clinically significant decreases in blood pressure. The clinical consequences of these hemodynamic effects, if any, have not been evaluated.

Effects on heart rate are variable, dependent upon rate of administration and presence of underlying cardiac condition. While increases in both peak positive dP/dt and LV ejection fraction are seen when intravenous isradipine is given, it is impossible to conclude that these represent a positive inotropic effect due to simultaneous changes in preload and afterload. In patients with coronary artery disease undergoing atrial pacing during cardiac catheterization, intravenous isradipine diminished abnormalities of systolic performance. In patients with moderate left ventricular dysfunction, oral and intravenous isradipine in doses which reduce blood pressure by 12%- 30%, resulted in improvement in cardiac index without increase in heart rate, and with no change or reduction in pulmonary capillary wedge pressure. Combination of isradipine and propranolol did not significantly affect left ventricular dP/dt max. The clinical consequences of these effects have not been evaluated.

Electrophysiologic Effects

In general, no detrimental effects on the cardiac conduction system were seen with the use of isradipine. Electrophysiologic studies were conducted on patients with normal sinus and atrioventricular node function. Intravenous isradipine in doses which reduce systolic blood pressure did not affect PR, QRS, AH* or HV* intervals.

No changes were seen in Wenckebach cycle length, atrial, and ventricular refractory periods. Slight prolongation of QTc interval of 3% was seen in one study. Effects on sinus node recovery time (CSNRT) were mild or not seen.

In patients with sick sinus syndrome, at doses which significantly reduced blood pressure, intravenous isradipine resulted in no depressant effect on sinus and atrioventricular node function.

*AH = conduction time from low right atrium to His bundle deflection, or AV nodal conduction time; HV = conduction time through His bundle and the bundle branch-Purkinje system.

Pharmacokinetics and Metabolism

Isradipine is 90%-95% absorbed and is subject to extensive first-pass metabolism, resulting in a bioavailability of about 15%-24%. Isradipine is detectable in plasma within 20 minutes after administration of single oral doses of 2.5-20 mg, and peak concentrations of approximately 1 ng/mL/mg dosed occur about 1.5 hours after drug administration. Administration of isradipine with food significantly increases the time to peak by about an hour, but has no effect on the total bioavailability (area under the curve) of the drug. Isradipine is 95% bound to plasma proteins. Both peak plasma concentration and AUC exhibit a linear relationship to dose over the 0-20 mg dose range. The elimination of isradipine is biphasic with an early half-life of 1 ½-2 hours, and a terminal half-life of about 8 hours. The total body clearance of isradipine is 1.4 L/min and the apparent volume of distribution is 3 L/kg.

Isradipine is completely metabolized prior to excretion, and no unchanged drug is detected in the urine. Six metabolites have been characterized in blood and urine, with the mono acids of the pyridine derivative and a cyclic lactone product accounting for >75% of the material identified. Approximately 60%-65% of an administered dose is excreted in the urine and 25%-30% in the feces. Mild renal impairment (creatinine clearance 30-80 mL/min) increases the bioavailability (AUC) of isradipine by 45%. Progressive deterioration reverses this trend, and patients with severe renal failure (creatinine clearance <10 mL/min) who have been on hemodialysis show a 20%-50% lower AUC than healthy volunteers. No pharmacokinetic information is available on drug therapy during hemodialysis. In elderly patients, Cmax and AUC are increased by 13% and 40%, respectively; in patients with hepatic impairment, Cmax and AUC are increased by 32% and 52%, respectively (see DOSAGE AND ADMINISTRATION).

INDICATIONS AND USAGE

Hypertension

Isradipine is indicated in the management of hypertension. It may be used alone or concurrently with thiazide-type diuretics.

CONTRAINDICATIONS

Isradipine is contraindicated in individuals who have shown hypersensitivity to any of the ingredients in the formulation.

WARNINGS

None

PRECAUTIONS

General

Blood Pressure: Because isradipine decreases peripheral resistance, like other calcium blockers isradipine may occasionally produce symptomatic hypotension. However, symptoms like syncope and severe dizziness have rarely been reported in hypertensive patients administered isradipine, particularly at the initial recommended doses (see DOSAGE AND ADMINISTRATION).

Use in Patients with Congestive Heart Failure: Although acute hemodynamic studies in patients with congestive heart failure have shown that isradipine reduced afterload without impairing myocardial contractility, it has a negative inotropic effect at high doses in vitro, and possibly in some patients. Caution should be exercised when using the drug in congestive heart failure patients, particularly in combination with a beta-blocker.

Drug Interactions

Nitroglycerin: Isradipine has been safely coadministered with nitroglycerin.

Hydrochlorothiazide: A study in normal healthy volunteers has shown that concomitant administration of isradipine and hydrochlorothiazide does not result in altered pharmacokinetics of either drug. In a study in hypertensive patients, addition of isradipine to existing hydrochlorothiazide therapy did not result in any unexpected adverse effects, and isradipine had an additional antihypertensive effect.

Propranolol: In a single dose study in normal volunteers, co-administration of propranolol had a small effect on the rate but no effect on the extent of isradipine bioavailability. Significant increases in AUC (27%) and Cmax (58%) and decreases in tmax (23%) of propranolol were noted in this study. However, concomitant administration of 5 mg b.i.d. isradipine and 40 mg b.i.d. propranolol to healthy volunteers under steady-state conditions had no relevant effect on either drug’s bioavailability. AUC and Cmax differences were <20% between isradipine given singly and in combination with propranolol, and between propranolol given singly and in combination with isradipine.

Cimetidine: In a study in healthy volunteers, a one-week course of cimetidine at 400 mg b.i.d. with a single 5 mg dose of isradipine on the sixth day showed an increase in isradipine mean peak plasma concentrations (36%) and significant increase in area under the curve (50%). If isradipine therapy is initiated in a patient currently receiving cimetidine, careful monitoring for adverse reactions is advised and downward dose adjustment may be required.

Rifampicin: In a study in healthy volunteers, a six-day course of rifampicin at 600 mg/day followed by a single 5 mg dose of isradipine resulted in a reduction in isradipine levels to below detectable limits. If rifampicin therapy is required, isradipine concentrations and therapeutic effects are likely to be markedly reduced or abolished as a consequence of increased metabolism and higher clearance of isradipine.

Warfarin: In a study in healthy volunteers, no clinically relevant pharmacokinetic or pharmacodynamic interaction between isradipine and racemic warfarin was seen when two single oral doses of warfarin (0.7 mg/kg body weight) were administered during 11 days of multiple-dose treatment with 5 mg b.i.d. isradipine. Neither racemic warfarin nor isradipine binding to plasma proteins in vitro was altered by the addition of the other drug.

Digoxin: The concomitant administration of isradipine and digoxin in a single-dose pharmacokinetic study did not affect renal, nonrenal and total body clearance of digoxin.

Fentanyl Anesthesia: Severe hypotension has been reported during fentanyl anesthesia with concomitant use of a beta blocker and a calcium channel blocker. Even though such interactions have not been seen in clinical studies with isradipine, an increased volume of circulating fluids might be required if such an interaction were to occur.

Carcinogenesis, Mutagenesis, Impairment of Fertility

Treatment of male rats for 2 years with 2.5, 12.5, or 62.5 mg/kg/day isradipine admixed with the diet (approximately 6, 31, and 156 times the maximum recommended daily dose based on a 50 kg man) resulted in dose dependent increases in the incidence of benign Leydig cell tumors and testicular hyperplasia relative to untreated control animals. These findings, which were replicated in a subsequent experiment, may have been indirectly related to an effect of isradipine on circulating gonadotropin levels in the rats; a comparable endocrine effect was not evident in male patients receiving therapeutic doses of the drug on a chronic basis. Treatment of mice for two years with 2.5, 15, or 80 mg/kg/day isradipine in the diet (approximately 6, 38, and 200 times the maximum recommended daily dose based on a 50 kg man) showed no evidence of oncogenicity. There was no evidence of mutagenic potential based on the results of a battery of mutagenic tests. No effect on fertility was observed in male and female rats treated with up to 60 mg/kg/day isradipine.

Pregnancy

Pregnancy Category C: Isradipine was administered orally to rats and rabbits during organogenesis. Treatment of pregnant rats with doses of 6, 20, or 60 mg/kg/day produced a significant reduction in maternal weight gain during treatment with the highest dose (150 times the maximum recommended human daily dose) but with no lasting effects on the mother or the offspring. Treatment of pregnant rabbits with doses of 1, 3, or 10 mg/kg/day (2.5, 7.5, and 25 times the maximum recommended human daily dose) produced decrements in maternal body weight gain and increased fetal resorption at the two higher doses. There was no evidence of embryotoxicity at doses which were not maternotoxic and no evidence of teratogenicity at any dose tested. In a peri/postnatal administration study in rats, reduced maternal body weight gain during late pregnancy at oral doses of 20 and 60 mg/kg/day isradipine was associated with reduced birth weights and decreased peri and postnatal pup survival.

There are no adequate and well controlled studies in pregnant women. The use of isradipine during pregnancy should only be considered if the potential benefit outweighs potential risks.

Nursing Mothers

It is not known whether isradipine is excreted in human milk. Because many drugs are excreted in human milk, and because of the potential for adverse effects of isradipine on nursing infants, a decision should be made as to whether to discontinue nursing or discontinue the drug, taking into account the importance of the drug to the mother.

Pediatric Use

Safety and effectiveness in pediatric patients have not been established.

ADVERSE REACTIONS

In multiple dose U.S. studies in hypertension, 1228 patients received isradipine alone or in combination with other agents, principally a thiazide diuretic, 934 of them in controlled comparisons with placebo or active agents. An additional 652 patients (which includes 374 normal volunteers) received isradipine in U.S. studies of conditions other than hypertension, and 1321 patients received isradipine in non-U.S. studies. About 500 patients received isradipine in long-term hypertension studies, 410 of them for at least 6 months. The adverse reaction rates given below are principally based on controlled hypertension studies, but rarer serious events are derived from all exposures to isradipine, including foreign marketing experience.

Most adverse reactions were mild and related to the vasodilatory effects of isradipine (dizziness, edema, palpitations, flushing, tachycardia), and many were transient. About 5% of isradipine patients left studies prematurely because of adverse reactions (vs. 3% of placebo patients and 6% of active control patients), principally due to headache, edema, dizziness, palpitations, and gastrointestinal disturbances.

The following table shows the most common adverse reactions, volunteered or elicited, considered by the investigator to be at least possibly drug related. The results for the isradipine treated patients are presented for all doses pooled together (reported by 1% or greater of patients receiving any dose of isradipine), and also for the two treatment regimens most applicable to the treatment of hypertension with isradipine: (1) initial and maintenance dose of 2.5 mg b.i.d., and (2) initial dose of 2.5 mg b.i.d. followed by maintenance dose of 5 mg b.i.d.

 |  | Isradipine
Adverse Experience | All Doses N=934 % | 2.5 mg b.i.d. 199 % | 5 mg b.i.d.† 150 % | 10 mg b.i.d.†† 59 % | Placebo % | Active Controls* 414 %
Headache Dizziness Edema Palpitations | 13.7 7.3 7.2 4.0 | 12.6 8.0 3.5 1.0 | 10.7 5.3 8.7 4.7 | 22.0 3.4 8.5 5.1 | 14.1 4.4 3.0 1.4 | 9.4 8.2 2.9 1.5
Fatigue Flushing Chest Pain Nausea | 3.9 2.6 2.4 1.8 | 2.5 3.0 2.5 1.0 | 2.0 2.0 2.7 2.7 | 8.5 5.1 1.7 5.1 | 0.3 0.0 2.4 1.7 | 6.3 1.2 2.9 3.1
Dyspnea Abdominal Discomfort Tachycardia Rash | 1.8 1.7 1.5 1.5 | 0.5 0.0 1.0 1.5 | 2.7 3.3 1.3 2.0 | 3.4 1.7 3.4 1.7 | 1.0 1.7 0.3 0.3 | 2.2 3.9 0.5 0.7
Pollakiuria Weakness Vomiting Diarrhea | 1.5 1.2 1.1 1.1 | 2.0 0.0 1.0 0.0 | 1.3 0.7 1.3 2.7 | 3.4 0.0 0.0 3.4 | 0.0 0.0 0.3 2.0 | <1.0 1.2 0.2 1.9

†Initial dose of 2.5 mg b.i.d. followed by maintenance dose of 5 mg b.i.d.

†† Initial dose of 2.5 mg b.i.d. followed by sequential titration to 5 mg b.i.d., 7.5 mg b.i.d., and maintenance dose of 10 mg b.i.d.

*Propranolol, prazosin, hydrochlorothiazide, enalapril, captopril.

Except for headache, which is not clearly drug-related (see previous table), the more frequent adverse reactions listed show little change, or increase slightly, in frequency over time, as shown in the following table:

Incidence Rates for Isradipine
(All Doses) by Week (%)
Week N | 1 694 | 2 906 | 3 649 | 4 847 | 5 432 | 6 494
Adverse Reaction
Headache Dizziness Edema Palpitations Fatigue Flushing | 6.5 1.6 1.2 1.2 0.4 1.2 | 6.1 1.9 2.5 1.3 1.0 1.3 | 5.2 1.7 3.2 1.4 1.4 2.0 | 5.2 2.2 3.2 1.9 1.2 1.4 | 5.8 2.3 5.3 2.1 1.2 2.1 | 4.5 2.0 5.5 1.4 1.6 1.4
Week N | 7 153 | 8 377 | 9 261 | 10 362 | 11 107 | 12 105
Adverse Reaction
Headache Dizziness Edema Palpitations Fatigue Flushing | 2.0 2.0 5.9 1.3 2.0 3.3 | 2.7 1.9 5.0 0.8 2.7 1.3 | 1.9 2.3 4.6 0.8 1.5 1.1 | 2.8 3.9 4.7 1.7 1.4 0.8 | 2.8 4.7 3.8 1.9 0.9 0.0 | 3.8 3.8 3.8 2.9 1.9 0.0

Edema, palpitations, fatigue, and flushing appear to be dose-related, especially at the higher doses of 15-20 mg/day.

In open-label, long-term studies of up to two years in duration, the adverse events reported were generally the same as those reported in the short-term controlled trials. The overall frequencies of these adverse events were slightly higher in the long-term than in the controlled studies, but as in the controlled trials most adverse reactions were mild and transient.

The following adverse experiences were reported in 0.5%-1.0% of the isradipine-treated patients in hypertension studies, or are rare. More serious events from this and other data sources, including postmarketing exposure, are shown in italics. The relationship of these adverse events to isradipine administration is uncertain.

Skin: pruritus, urticaria

Musculoskeletal: cramps of legs/feet

Respiratory: cough

Cardiovascular: shortness of breath, hypotension, atrial fibrillation, ventricular fibrillation, myocardial infarction, heart failure

Gastrointestinal: abdominal discomfort, constipation, diarrhea

Urogenital: nocturia

Nervous System: drowsiness, insomnia, lethargy, nervousness, impotence, decreased libido, depression, syncope, paresthesia (which includes numbness and tingling), transient ischemic attack, stroke

Autonomic: hyperhidrosis, visual disturbance, dry mouth, numbness

Miscellaneous: throat discomfort, leukopenia, elevated liver function tests

To report SUSPECTED ADVERSE REACTIONS, contact AvKARE at 1-855-361-3993 or FDA at 1-800-FDA-1088 or www.fda.gov/medwatch.

OVERDOSAGE

Minimal empirical data are available on isradipine overdosage. Three individual suicide attempts with dosages of isradipine reported to be from 20 mg up to 100 mg resulted in lethargy, sinus tachycardia and, in the case of the person ingesting 100 mg, transient hypotension which responded to fluid therapy. A foreign report of the ingestion of 200 mg of isradipine with ethanol resulted only in flushing, tachycardia with ST depression on ECG, and hypotension, all of which were reversible. The ingestion of 5 mg of isradipine by a 22-month old child and the accidental ingestion of 100 mg of isradipine by a 58-year old female did not result in any sequelae.

Available data suggest that, as with other dihydropyridines, overdosage with isradipine might result in excessive peripheral vasodilatation with subsequent marked and probably prolonged systemic hypotension, and tachycardia. Emesis, gastric lavage, administration of activated charcoal followed in 30 minutes by a saline cathartic would be reasonable therapy. Isradipine is highly protein-bound and not removed by hemodialysis. Overdosage characterized by clinically significant hypotension should be treated with active cardiovascular support including monitoring of cardiac and respiratory function, elevation of lower extremities, and attention to circulating fluid volume and urine output. A vasoconstrictor (such as epinephrine, norepinephrine, or levarterenol) may be helpful in restoring a normotensive state, provided that there is no contraindication to its use.

Refractory hypotension or AV conduction disturbances may be treated with intravenous calcium salts, or glucagon. Cimetidine should be withheld in such instances due to the risk of further increasing plasma isradipine levels.

Significant lethality was observed in mice given oral doses of over 200 mg/kg and rabbits given about 50 mg/kg of isradipine. Rats tolerated doses of over 2000 mg/kg without effects on survival.

DOSAGE AND ADMINISTRATION

The dosage of isradipine should be individualized. The recommended initial dose of isradipine is 2.5 mg b.i.d. alone or in combination with a thiazide diuretic. An antihypertensive response usually occurs within 2-3 hours. Maximal response may require 2-4 weeks. If a satisfactory reduction in blood pressure does not occur after this period, the dose may be adjusted in increments of 5 mg/day at 2-4 week intervals up to a maximum of 20 mg/day. Most patients, however, show no additional response to doses above 10 mg/day, and adverse effects are increased in frequency above 10 mg/day.

The bioavailability of isradipine (increased AUC) is increased in elderly patients (above 65 years of age), patients with hepatic functional impairment, and patients with mild renal impairment. Ordinarily, the starting dose should still be 2.5 mg b.i.d. in these patients.

HOW SUPPLIED

Isradipine Capsules, USP

2.5 mg
Brown opaque, imprinted with “ ” IS 2.5.

Bottles of 100 capsules (NDC 42291-062-01)

5 mg
Caramel opaque, imprinted with “ ” IS 5.

Store and Dispense

Store at 20°-25°C (68°-77°F) [See USP Controlled Room Temperature] and dispense in a tight, light-resistant container

Rx Only

Manufactured for:
AvKARE
Pulaski, TN 38478

Mfg. Rev. 06/17
AV 05/23 (P)